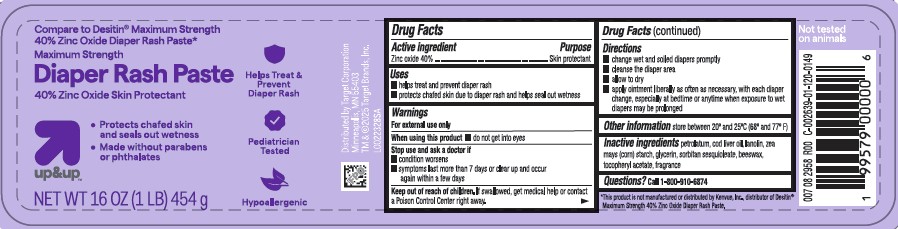 DRUG LABEL: Diaper Rash
NDC: 11673-020 | Form: PASTE
Manufacturer: Target Corporation
Category: otc | Type: HUMAN OTC DRUG LABEL
Date: 20260218

ACTIVE INGREDIENTS: ZINC OXIDE 400 mg/1 g
INACTIVE INGREDIENTS: PETROLATUM; COD LIVER OIL; LANOLIN; STARCH, CORN; GLYCERIN; SORBITAN SESQUIOLEATE; YELLOW WAX; .ALPHA.-TOCOPHEROL ACETATE

Up & Up 020.002/020AC-AD
Diaper Rash Ointment 40% Zinc Oxide

Active ingredient

Zinc oxide 40%

Purpose

Skin Protectant

Uses

• helps treat and prevent diaper rash
• protects chafed skin due to the diaper rash and helps seal out wetness

Warnings

For external use only

When using this product

- do not get into eyes

Stop use and ask a doctor if

- condition worsens
- symptoms last more than 7 days or clear up and occur again within a few days

Keep out of reach of children.

If swallowed, get medical help or contact a Poison Control Center right away.

Directions

- change wet and soiled diapers promptly
- cleanse the diaper area
- allow to dry
- apply ointment liberally as often as necessary, with each diaper change, especially at bedtime or anytime when exposure to wet diapers may be prolonged

Other information

• store between 20⁰ and 25⁰C (68⁰ and 77⁰F)

Inactive ingredients

petrolatum, cod liver oil, lanolin, Zea mays (corn) starch, glycerin, sorbitan sesquioleate, beeswax, tocopheryl acetate, fragrance

Questions

Call 1-800-910-6874

Claims

*This product is not manufactured or distributed by Kenvue, Inc., distributor of Destin®Maximum Strength 40% Zinc Oxide Diaper Rash Paste.

Adverse Reactions

Distributed by Target Corporation

Minneapolis, MN 55403

TM & © 2025 Target Brands, Inc.

Not tested on animals

Principal display panel

Compare to Desitin® Maximum Strength 40% Zinc Oxide Diaper Rash Paste*

Maximum Strength

Diaper Rash Paste

40% Zinc Oxide Skin Protectant

- Protects chafed skin and seals out wetness
- Made without parabens or phthalates

Helps Treat & Prevent Diaper Rash

Pediatrician Tested

Hypoallergenic

up & up™

NET WT 16 OZ (454 g)